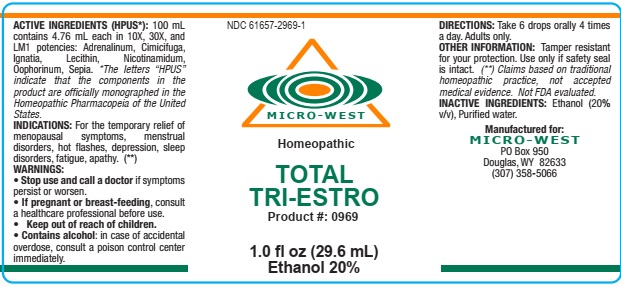 DRUG LABEL: TOTAL TRI-ESTRO
NDC: 61657-2969 | Form: LIQUID
Manufacturer: White Manufacturing Inc. DBA Micro-West
Category: homeopathic | Type: HUMAN PRESCRIPTION DRUG LABEL
Date: 20210121

ACTIVE INGREDIENTS: EPINEPHRINE 10 [hp_X]/30 mL; BLACK COHOSH 10 [hp_X]/30 mL; STRYCHNOS IGNATII SEED 10 [hp_X]/30 mL; EGG PHOSPHOLIPIDS 10 [hp_X]/30 mL; NIACINAMIDE 10 [hp_X]/30 mL; SUS SCROFA OVARY 10 [hp_X]/30 mL; SEPIA OFFICINALIS JUICE 10 [hp_X]/30 mL
INACTIVE INGREDIENTS: ALCOHOL; WATER

TOTAL TRI-ESTRO

ACTIVE INGREDIENTS (HPUS*): 100 mL
contains 4.76 mL each in 10X, 30X, and
LM1 potencies: Adrenalinum, Cimicifuga,
Ignatia, Lecithin, Nicotinamidum,
Oophorinum, Sepia. *The letters “HPUS”
indicate that the components in the
product are officially monographed in the
Homeopathic Pharmacopeia of the United
States

INDICATIONS: For the temporary relief of
menopausal symptoms, menstrual
disorders, hot flashes, depression, sleep
disorders, fatigue, apathy. (**)

WARNINGS:
• Stop use and call a doctor if symptoms
persist or worsen.
• If pregnant or breast-feeding, consult
a healthcare professional before use.
• Keep out of reach of children.
• Contains alcohol: in case of accidental
overdose, consult a poison control center
immediately

• Keep out of reach of children.

DOSAGE AND ADMINISTRATION

DIRECTIONS: Take 6 drops orally 4 times
a day. Adults only.

OTHER INFORMATION: Tamper resistant
for your protection. Use only if safety seal
is intact. (**) Claims based on traditional
homeopathic practice, not accepted
medical evidence. Not FDA evaluated.

INACTIVE INGREDIENTS: Ethanol (20%
v/v), Purified water.

QUESTIONS

Manufactured for:
MICRO-WEST
PO Box 950
Douglas, WY 82633
(307) 358-5066

PACKAGE LABEL

NDC 61657-2969-1

MICRO-WEST

Homeopathic

TOTAL

TRI-ESTRO

Product #: 0969

1.0 fl oz (29.6 mL)

Ethanol 20%

PURPOSE

For the temporary relief of
menopausal symptoms, menstrual
disorders, hot flashes, depression, sleep
disorders, fatigue, apathy. (**)